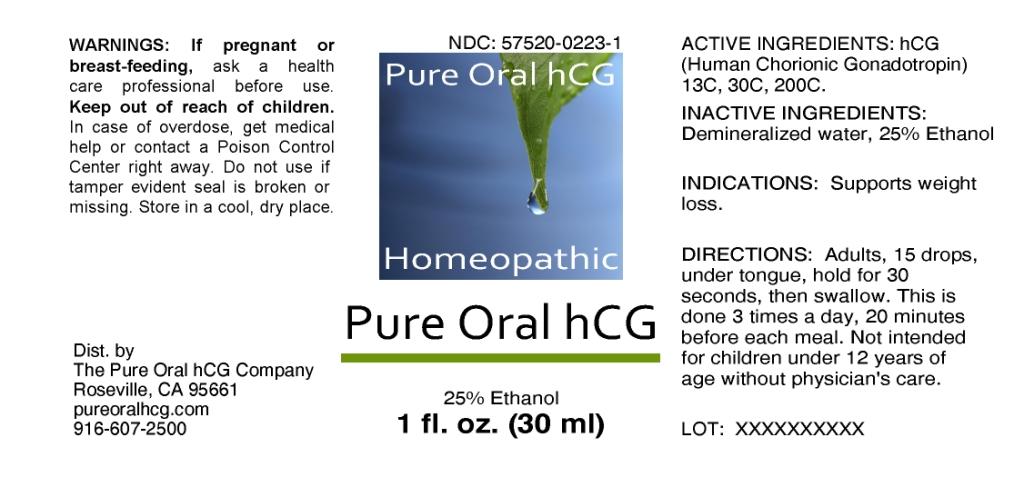 DRUG LABEL: Pure Oral hCG
NDC: 57520-0223 | Form: LIQUID
Manufacturer: Apotheca Company
Category: homeopathic | Type: HUMAN OTC DRUG LABEL
Date: 20100810

ACTIVE INGREDIENTS: HUMAN CHORIONIC GONADOTROPIN 200 [hp_C]/1 mL
INACTIVE INGREDIENTS: WATER; ALCOHOL

Pure Oral hCG

ACTIVE INGREDIENT

ACTIVE INGREDIENTS: hCG(Human Chorionic Gonadotropin) 13C, 30C, 200C.

PURPOSE

INDICATIONS: Supports weight loss.

WARNINGS

WARNINGS: If pregnant or breast-feeding, ask a health care professional before use.

Keep out of reach of children. In case of overdose, get medical help or contact a Poison Control Center right away.

Do not use if tamper evident seal is broken or missing. Store in a cool, dry place.

DOSAGE AND ADMINISTRATION

DIRECTIONS: Adults, 15 drops, under tongue, hold for 30 seconds, then swallow. This is done 3 times a day, 20 minutes before each meal. Not intended for children under 12 years of age without physician's care.

INACTIVE INGREDIENTS: Demineralized water, 25% Ethanol.

QUESTIONS

Dist. by:

The Pure Oral hCG Company

Roseville, CA 95661

916-607-2500

PACKAGE LABEL

Pure Oral hCG

Homeopathic

Pure Oral hCG

1 fl -z (30 ml)